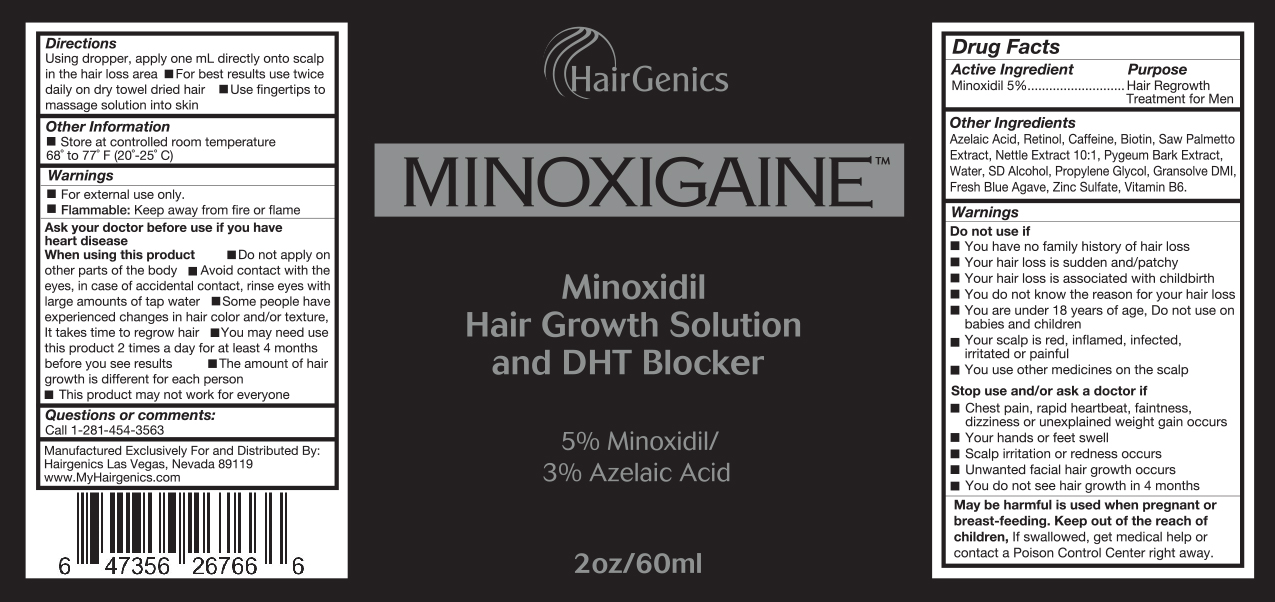 DRUG LABEL: MINOXIGAINE
NDC: 72965-001 | Form: LIQUID
Manufacturer: Hairgenics LLC
Category: otc | Type: HUMAN OTC DRUG LABEL
Date: 20190326

ACTIVE INGREDIENTS: MINOXIDIL 50 mg/1 mL
INACTIVE INGREDIENTS: AZELAIC ACID; RETINOL; CAFFEINE; BIOTIN; SAW PALMETTO; URTICA DIOICA; PYGEUM; WATER; ALCOHOL; PROPYLENE GLYCOL; DIMETHYL ISOSORBIDE; AGAVE TEQUILANA LEAF; ZINC SULFATE; PYRIDOXINE

ACTIVE INGREDIENT

Minoxidil 5%

PURPOSE

Hair Regrowth Treatment for Men

WARNINGS

For external use only.
Flammable: Keep away from fire or flame
Do not use if:
• You have no family history of hair loss
• Your hair loss is sudden and/or patchy

• Your hair loss is associated with childbirth
• You do not know the reason for your hair loss
• You are under 18 years of age. Do not use on babies and children
• Your scalp is red, inflamed, irritated or painful
• You use other medicines on the scalp
Ask a doctor before use if you have heart disease
When using this product
• Do not apply on other parts of the body
• Avoid contact with the eyes. In case of accidental contact, rinse eyes with large amounts of tap water
• Some people have experienced changes in hair color and/or texture it takes time to regrow hair.
• You may need to use this product 2 times a day for at least 4 months before you see results
• The amount of hair regrowth is different for each person.
• This product may not work for everyone.
Stop use and/or ask a doctor if
• Chest pain, rapid heartbeat, faintness, dizziness or unexplained weight gain occurs
• Your hands or feet swell
• Scalp irritation or redness occurs
• Unwanted facial hair growth occurs
• You do not see hair regrowth in 4 months
May be harmful is used when pregnant or breast-feeding.

Keep out of reach of children. If swallowed, get medical help or contact a Poison Control Center right away.

Directions

Using dropper, apply one mL directly onto the scalp in the hair loss area

For best results use twice daily on dry towel dried hair.

Use fingertips to massage solution into skin

Other Information

• Store at controlled room temperature 68º to 77ºF (20º- 25ºC)

Other Ingredients

Azelaic Acid, Retinol, Caffeine, Biotin, Saw Palmetto Extract, Nettle Extract 10:1, Pygeum Bark Extract, Water, SD Alcohol, Propylene Glycol, Gransolve DMI, Fresh Blue Agave, Zinc Sulfate, Vitamin B6.

Questions or comments:
1-281-454-3563